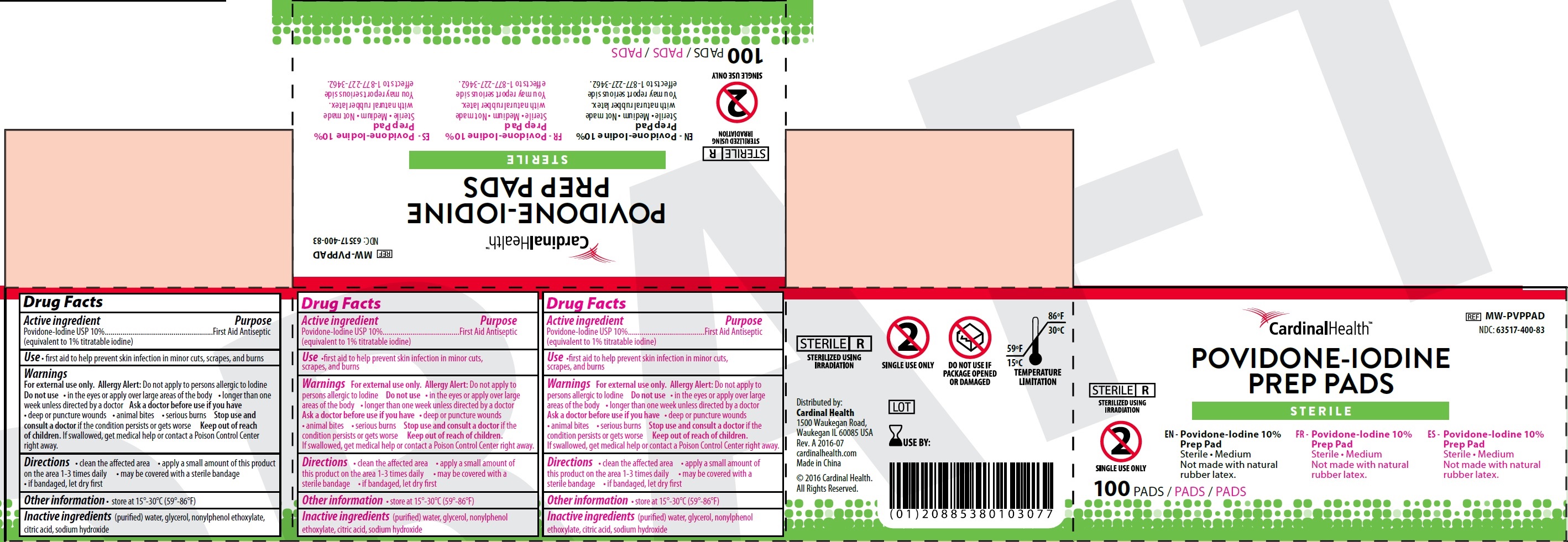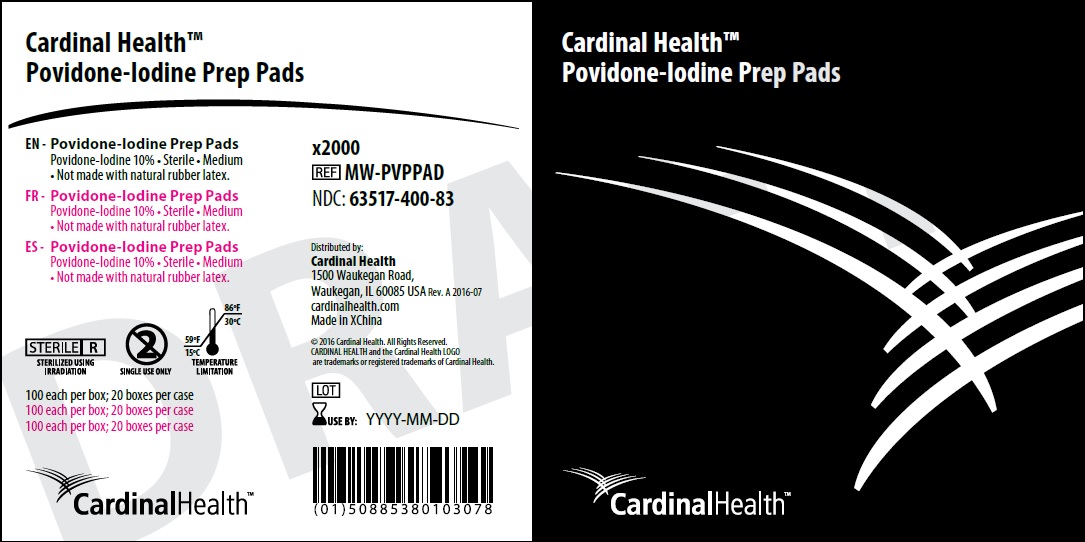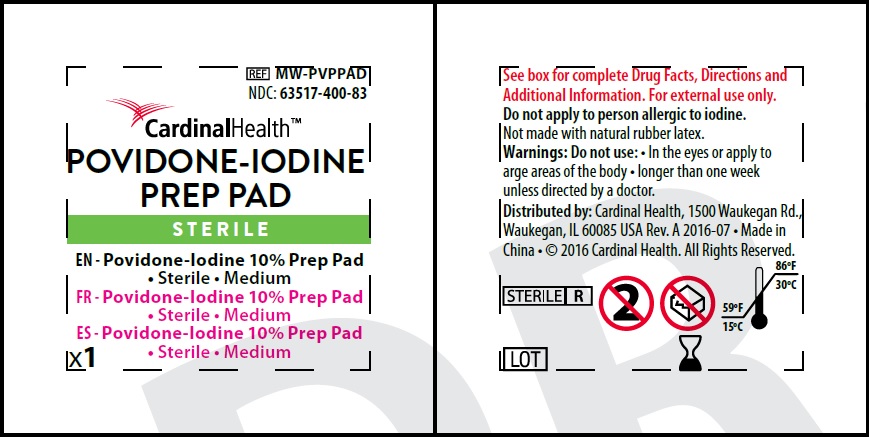 DRUG LABEL: Povidone-Iodine Prep Pad
NDC: 63517-400 | Form: SOLUTION
Manufacturer: Cardinal Health 200, Inc.
Category: otc | Type: HUMAN OTC DRUG LABEL
Date: 20231023

ACTIVE INGREDIENTS: POVIDONE-IODINE 10 g/100 g
INACTIVE INGREDIENTS: WATER; GLYCERIN; CITRIC ACID MONOHYDRATE; SODIUM HYDROXIDE

Povidone-Iodine Prep Pad

Active ingredient

Povidone-Iodine USP 10% (equivalent to 1% titratable iodine)

Purpose

First Aid Antiseptic

Use

•first aid to help prevent skin infection in minor cuts, scrapes, and burns

Warnings

For external use only. Do not apply to persons allergic to Iodine Allergy Alert:

Do not use

• in the eyes or apply over large areas of the body • longer than one week unless directed by a doctor

Ask a doctor before use if you have

• deep or puncture wounds • animal bites • serious burns

Stop use and consult a doctor

if the condition persists or gets worse

Keep out of reach of children.

If swallowed, get medical help or contact a Poison Control Center right away.

Directions

• clean the affected area • apply a small amount of this product on the area 1-3 times daily • may be covered with a sterile bandage • if bandaged, let dry first

Other information

• store at 15°-30°C (59°-86°F)

Inactive ingredients

(purified) water, glycerol, nonylphenol ethoxylate, citric acid, sodium hydroxide

Package Labeling:

Packet Labeling:

Box Labeling:

Carton Labeling: